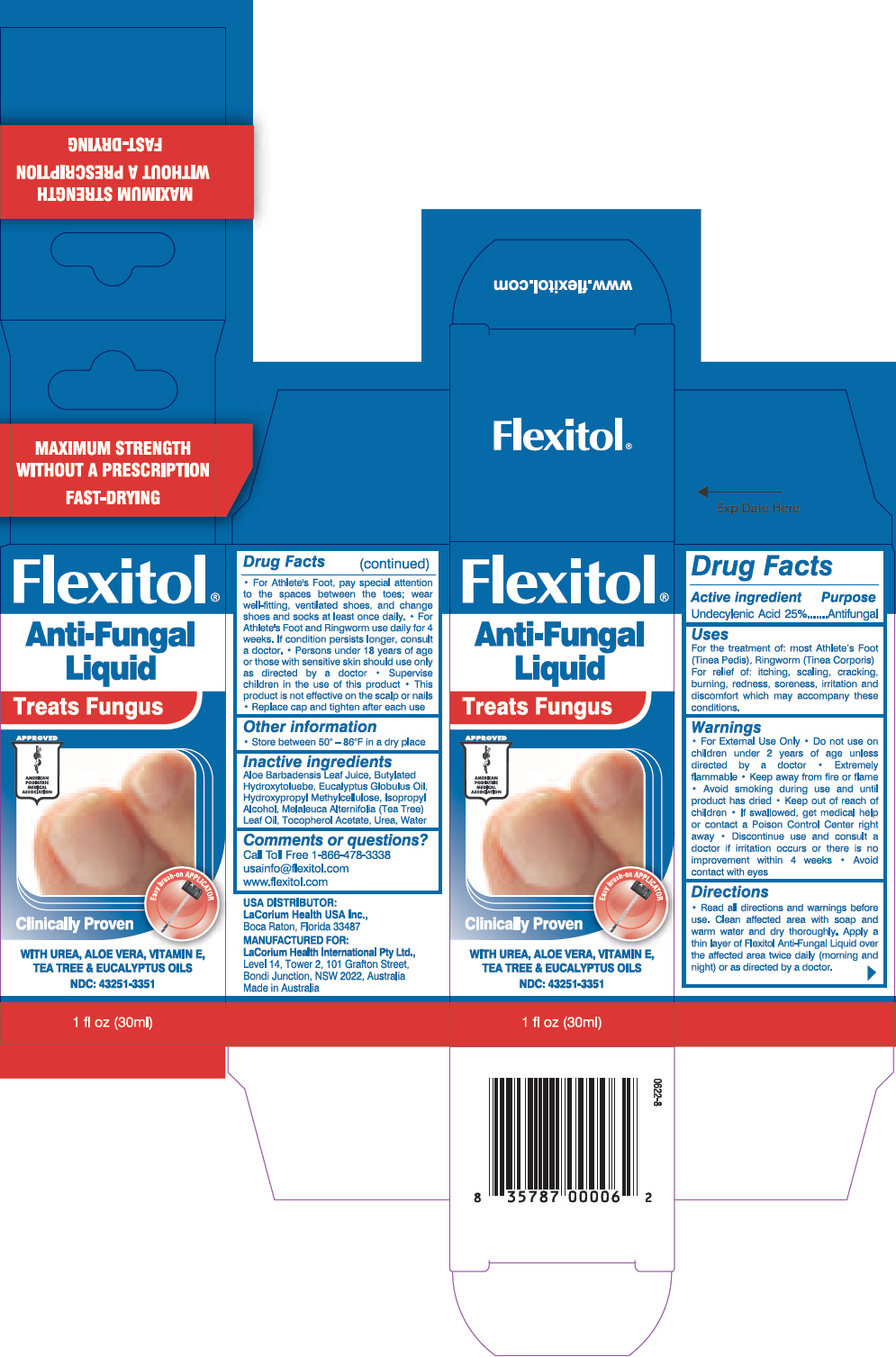 DRUG LABEL: Flexitol Anti Fungal
NDC: 43251-3351 | Form: LIQUID
Manufacturer: LaCorium Health International Pty Ltd
Category: otc | Type: HUMAN OTC DRUG LABEL
Date: 20121220

ACTIVE INGREDIENTS: Undecylenic acid 250 mg/1 mL
INACTIVE INGREDIENTS: Isopropyl Alcohol; Water; Urea; Eucalyptus Oil; Hypromellose 2906 (4000 MPA.S); Tea Tree Oil; .Alpha.-Tocopherol Acetate, DL-; Aloe Vera Leaf; Butylated Hydroxytoluene

Flexitol®
Anti-Fungal Liquid

Drug Facts

Active ingredient

Undecylenic Acid 25%

Purpose

Antifungal

Uses

For the treatment of: most Athlete's Foot (Tinea Pedis), Ringworm (Tinea Corporis). For relief of: itching, scaling, cracking, burning, redness, soreness, irritation and discomfort which may accompany these conditions.

Warnings

- For external use only

- Do not use on children under 2 years of age unless directed by a doctor

WHEN USING

- Extremely flammable
- Keep away from fire or flame
- Avoid smoking during use and until product has dried

- Keep out of reach of children
- If swallowed, get medical help or contact a Poison Control Center right away

STOP USE

- Discontinue use and consult a doctor if irritation occurs or there is no improvement within 4 weeks

Directions

- Read all directions and warnings before use
- Clean affected area with soap and warm water and dry thoroughly
- Apply a thin layer of Flexitol Anti-Fungal Liquid over the affected area twice daily (morning and night) or as directed by a doctor
- For Athlete's Foot, pay special attention to the spaces between the toes; wear well-fitting, ventilated shoes, and change shoes and socks at least once daily.
- For Athlete's Foot and Ringworm use daily for 4 weeks. If condition persists longer, consult a doctor.
- Persons under 18 years of age or those with sensitive skin should use only as directed by a doctor
- Supervise children in the use of this product
- This product is not effective on the scalp or nails
- Replace cap and tighten after each use

Other information

Store between 50° – 86°F in a dry place

Inactive ingredients

Aloe Barbadensis Leaf Juice, Butylated Hydroxytoluebe, Eucalyptus Globulus Oil, Hydroxypropyl Methylcellulose, Isopropyl Alcohol, Melaleuca Alternifolia (Tea Tree) Leaf Oil, Tocopherol Acetate, Urea, Water

Comments or questions?

Call Toll Free 1-866-478-3338
usainfo@flexitol.com
www.flexitol.com

PRINCIPAL DISPLAY PANEL - 30ml Bottle Carton

Flexitol®

Anti-Fungal
Liquid

Treats Fungus

APPROVED
AMERICAN
PODIATRIC
MEDICAL
ASSOCIATION

Clinically Proven

Easy brush-on APPLICATOR

WITH UREA, ALOE VERA, VITAMIN E,
TEA TREE & EUCALYPTUS OILS

NDC: 43251-3351

1 fl oz (30ml)